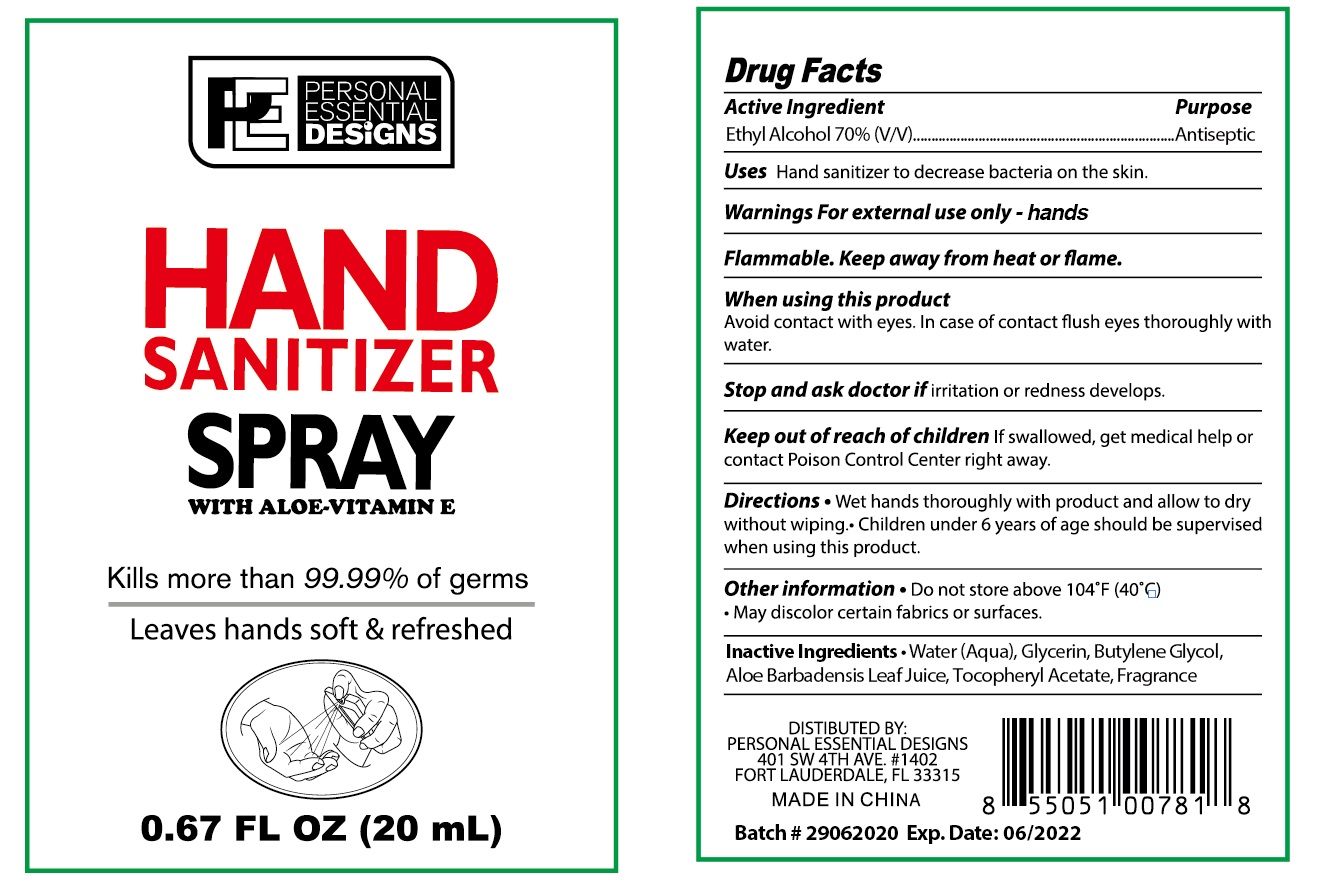 DRUG LABEL: hand sanitizer
NDC: 50049-123 | Form: SPRAY
Manufacturer: QUANZHOU BESTHOPE HOUSEHOLD PRODUCTS CO.,LTD.
Category: otc | Type: HUMAN OTC DRUG LABEL
Date: 20200609

ACTIVE INGREDIENTS: ALCOHOL 70 mL/100 mL
INACTIVE INGREDIENTS: ALPHA-TOCOPHEROL ACETATE; WATER; GLYCERIN; ALOE VERA LEAF; BUTYLENE GLYCOL

50049-123 Hand Sanitizer Spray

Active Ingredient

Ethyl Alcohol 70%

Purpose

Antiseptic

Use

Uses Hand sanitizer to decrease bacteria on the skin.

Warnings For external use only - hands
Flammable. Keep away from heat or flame.
When using this product
Avoid contact with eyes. In case of contact flush eyes thoroughly with
water.
Stop and ask doctor if irritation or redness develops.

Keep out of reach of children If swallowed, get medical help or
contact Poison Control Center right away.

Directions

Wet hands thoroughly with product and allow to dry
without wiping. Children under 6 years of age should be supervised
when using this product.

Inactive ingredients

Water (Aqua), Glycerin, Butylene Glycol,
Aloe Barbadensis Leaf Juice, Tocopheryl Acetate, Fragrance